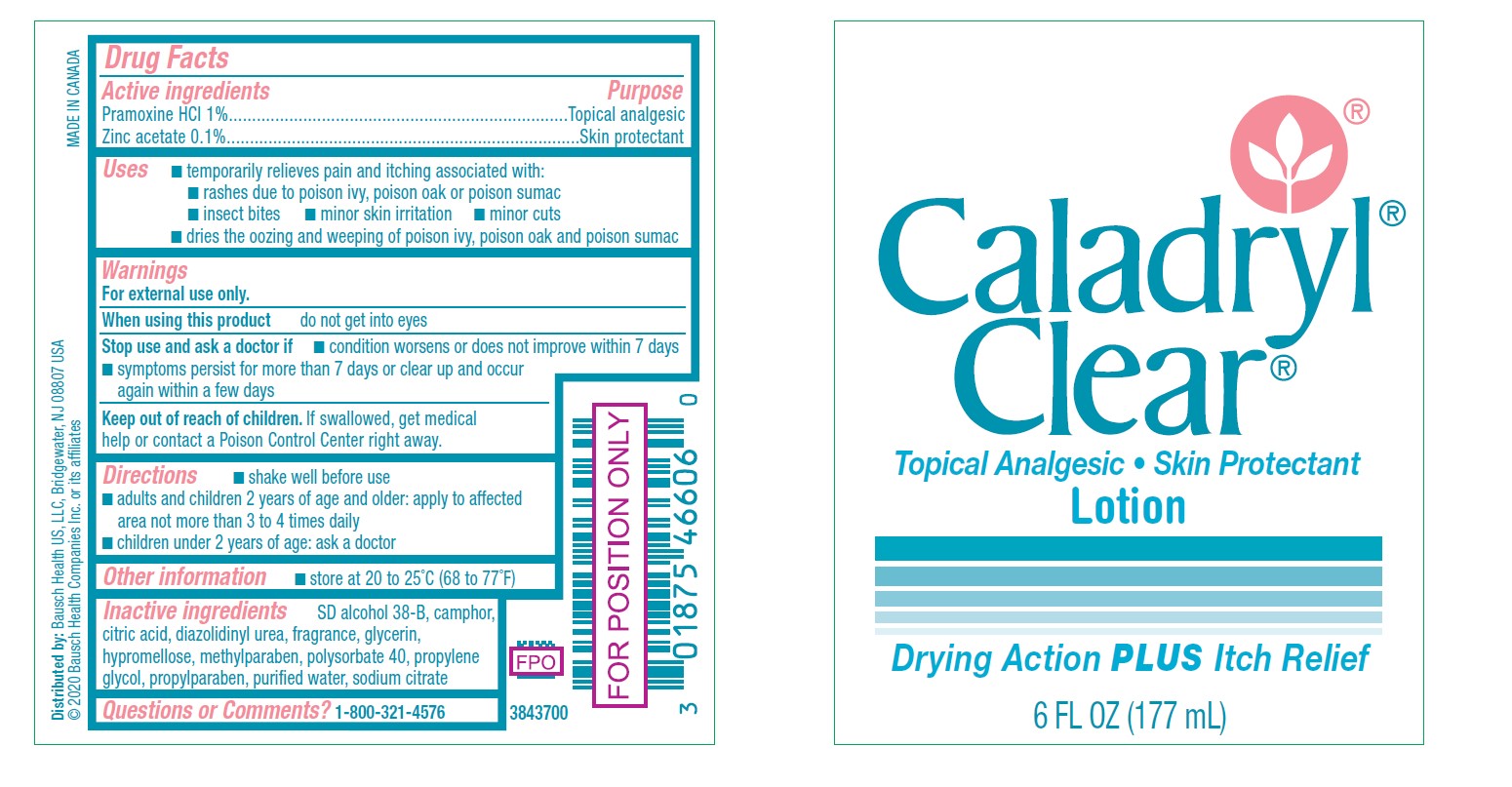 DRUG LABEL: Caladryl Clear
NDC: 0187-5466 | Form: LOTION
Manufacturer: Bausch Health US, LLC
Category: otc | Type: HUMAN OTC DRUG LABEL
Date: 20241017

ACTIVE INGREDIENTS: PRAMOXINE HYDROCHLORIDE 10 mg/1 mL; ZINC ACETATE 1 mg/1 mL
INACTIVE INGREDIENTS: CAMPHOR (SYNTHETIC); CITRIC ACID MONOHYDRATE; DIAZOLIDINYL UREA; GLYCERIN; METHYLPARABEN; POLYSORBATE 40; PROPYLENE GLYCOL; PROPYLPARABEN; WATER; HYPROMELLOSE, UNSPECIFIED; SODIUM CITRATE, UNSPECIFIED FORM

Caladryl Clear

Drug Facts

ACTIVE INGREDIENT

Active ingredients | Purpose
Pramoxine HCl 1% | Topical analgesic
Zinc acetate 0.1% | Skin protectant

Uses

- temporarily relieves pain and itching associated with:
  - rashes due to poison ivy, poison oak or poison sumac
  - insect bites
  - minor skin irritation
  - minor cuts
- dries the oozing and weeping of poison ivy, poison oak and poison sumac

Warnings

For external use only.

When using this productdo not get into eyes

STOP USE

Stop use and ask a doctor if

- condition worsens or does not improve within 7 days
- symptoms persist for more than 7 days or clear up and occur again within a few days

Keep out of reach of children.If swallowed, get medical help or contact a Poison Control Center right away.

Directions

- shake well before use
- adults and children 2 years of age and older: apply to affected area not more than 3 to 4 times daily
- children under 2 years of age: ask a doctor

Other information

- store at 20° to 25°C (68° to 77°F)

Inactive ingredients

SD alcohol 38-B, camphor, citric acid, diazolidinyl urea, fragrance, glycerin, hypromellose, methylparaben, polysorbate 40, propylene glycol, propylparaben, purified water, sodium citrate

Questions/Comments

call 1-800-321-4576

Distributed by:Bausch Health US, LLC, Bridgewater, NJ 08807 USA

© 2020 Bausch Health Companies Inc. or its affiliates

Rev. 01/2020
Made in Canada

PRINCIPAL DISPLAY PANEL - 177 mL Bottle Label

Caladryl®
Clear®
Topical Analgesic ∙ Skin Protectant
Lotion

Drying Action PLUSItch Relief

6 FL OZ (177 mL)